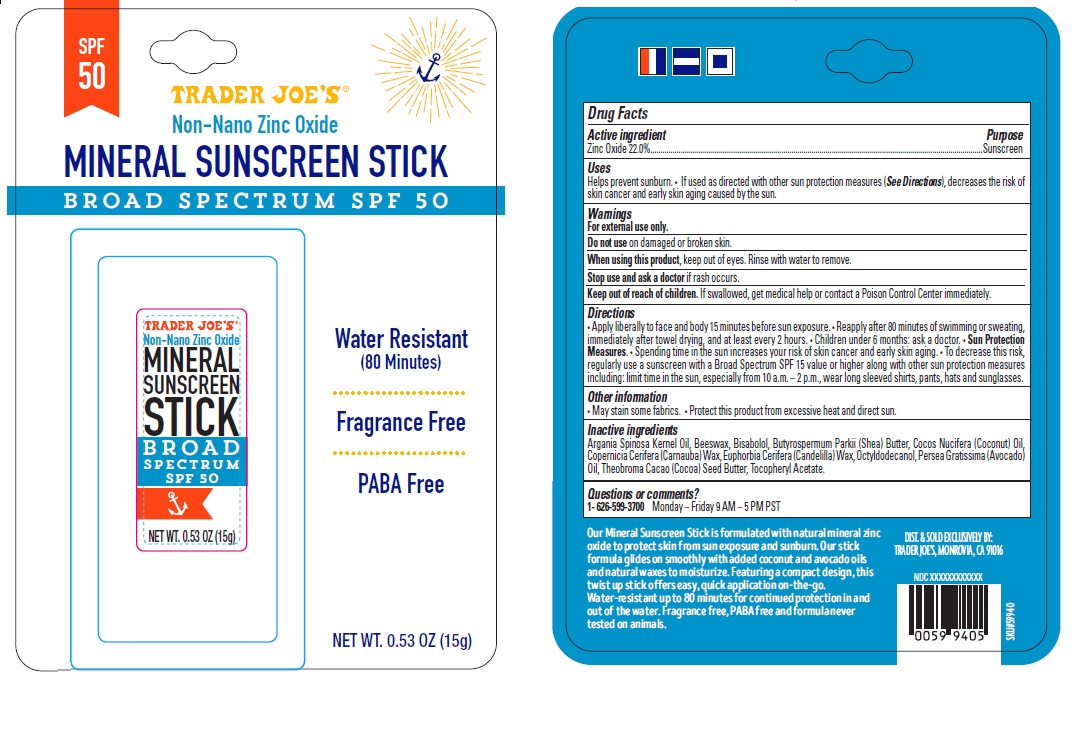 DRUG LABEL: TRADER JOE S MINERAL SUNSCREEN
NDC: 71270-150 | Form: STICK
Manufacturer: Trader Joe's Company
Category: otc | Type: HUMAN OTC DRUG LABEL
Date: 20170225

ACTIVE INGREDIENTS: ZINC OXIDE 22 g/100 g
INACTIVE INGREDIENTS: ARGAN OIL; YELLOW WAX; LEVOMENOL; SHEA BUTTER; COCONUT OIL; CARNAUBA WAX; CANDELILLA WAX; OCTYLDODECANOL; AVOCADO OIL; COCOA BUTTER; .ALPHA.-TOCOPHEROL ACETATE

TRADER JOE’S MINERAL SUNSCREEN STICK

Active ingredient

Zinc Oxide 22.0%

Purpose

Sunscreen

Uses

Helps prevent sunburn. • If used as directed with other sun protection measures (See Directions), decreases the risk of skin cancer and early skin aging caused by the sun.

Warnings

For external use only.

Do not use on damaged or broken skin.

When using this product, keep out of eyes. Rinse with water to remove.

Stop use and ask a doctor if rash occurs.

Keep out of reach of children. If swallowed, get medical help or contact a Poison Control Center immediately.

Directions

• Apply liberally to face and body 15 minutes before sun exposure. • Reapply after 80 minutes of swimming or sweating, immediately after towel drying, and at least every 2 hours. • Children under 6 months: ask a doctor. • Sun Protection Measures. • Spending time in the sun increases your risk of skin cancer and early skin aging. • To decrease this risk, regularly use a sunscreen with a Broad Spectrum SPF 15 value or higher along with other sun protection measures including: limit time in the sun, especially from 10 a.m. – 2 p.m., wear long sleeved shirts, pants, hats and sunglasses.

Other information

• May stain some fabrics. • Protect this product from excessive heat and direct sun.

Inactive ingredients

Argania Spinosa Kernel Oil, Beeswax, Bisabolol, Butyrospermum Parkii (Shea) Butter, Cocos Nucifera (Coconut) Oil, Copernicia Cerifera (Carnauba) Wax, Euphorbia Cerifera (Candelilla) Wax, Octyldodecanol, Persea Gratissima (Avocado) Oil, Theobroma Cacao (Cocoa) Seed Butter, Tocopheryl Acetate.

Questions or comments?

1- 626-599-3700 Monday – Friday 9 AM – 5 PM PST

Non-Nano Zinc Oxide

BROAD SPECTRUM SPF 50

Water Resistant
(80 Minutes)

Fragrance Free

PABA Free

Our Mineral Sunscreen Stick is formulated with natural mineral zinc oxide to protect skin from sun exposure and sunburn. Our stick formula glides on smoothly with added coconut and avocado oils and natural waxes to moisturize. Featuring a compact design, this twist up stick offers easy, quick application on-the-go.

Water-resistant up to 80 minutes for continued protection in and out of the water. Fragrance free, PABA free and formula never tested on animals.

DIST. & SOLD EXCLUSIVELY BY:

TRADER JOE’S, MONROVIA, CA 91016